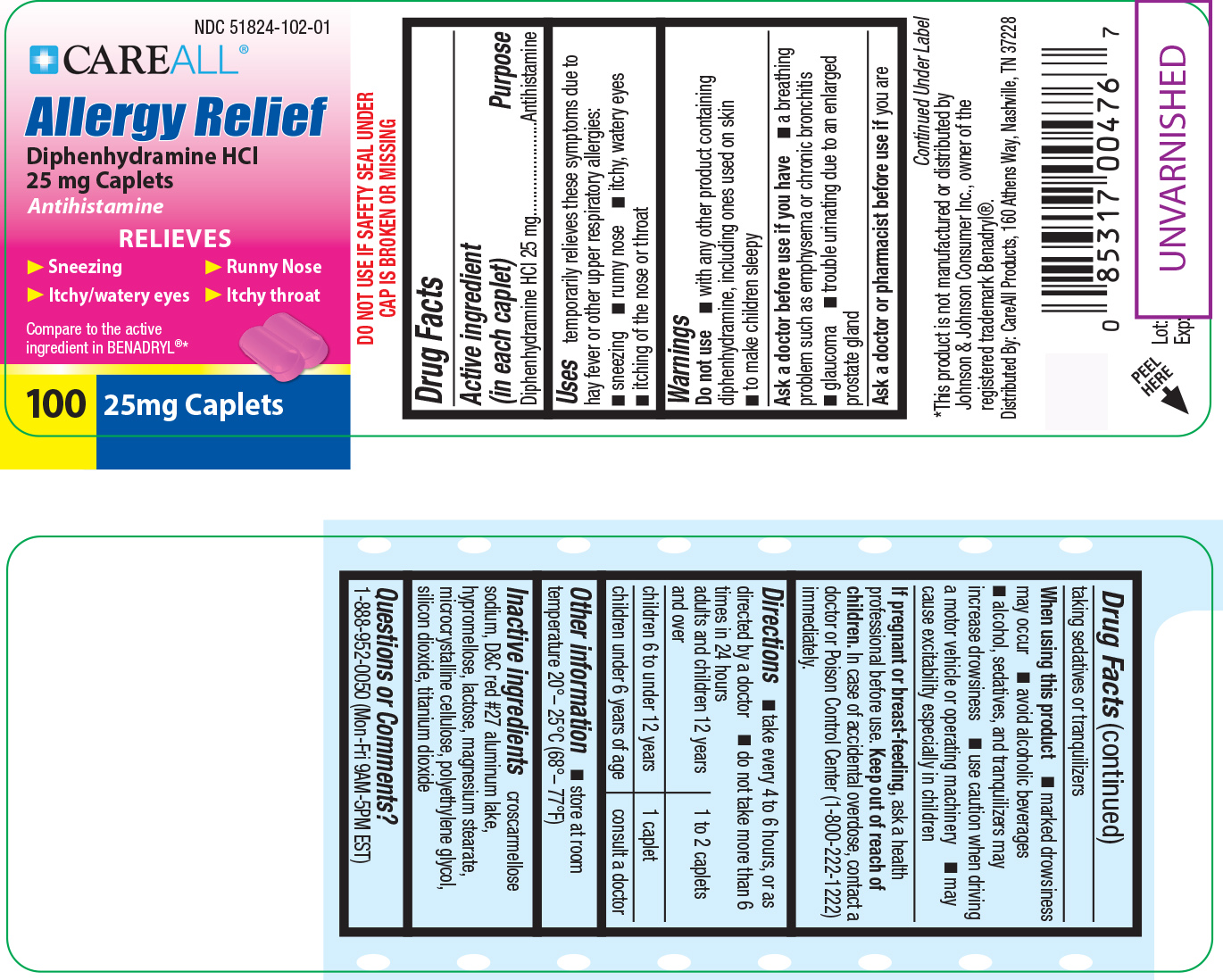 DRUG LABEL: CAREALL Allergy Relief
NDC: 51824-102 | Form: TABLET, COATED
Manufacturer: New World Imports, Inc
Category: otc | Type: HUMAN OTC DRUG LABEL
Date: 20251222

ACTIVE INGREDIENTS: DIPHENHYDRAMINE HYDROCHLORIDE 25 mg/1 1
INACTIVE INGREDIENTS: CROSCARMELLOSE SODIUM; D&C RED NO. 27 ALUMINUM LAKE; HYPROMELLOSE, UNSPECIFIED; LACTOSE, UNSPECIFIED FORM; MAGNESIUM STEARATE; CELLULOSE, MICROCRYSTALLINE; POLYETHYLENE GLYCOL, UNSPECIFIED; SILICON DIOXIDE; TITANIUM DIOXIDE

Drug Facts

Active Ingredient

Diphenhydramine HCl 25mg

Purpose

Antihistamine

Keep out of reach of children

In case of accidental overdose, contact a doctor or Poison Control Center (1-800-222-1222) immediately.

Uses

Temporarily relieves these symptoms due to hay fever or other upper respiratory allergies:

Sneezing, runny nose, itchy / watery eyes, and itching of the nose or throat

Warnings

Do not use

with any other products containing diphenhydramine, including ones used on skin

to make children sleepy

Ask a doctor before use if you have:

A breathing problem such as emphysema or chronic bronchitis

Glaucoma

Trouble urinating due to an enlarged prostate gland

Ask a doctor or pharmacist before use if youare taking sedatives or tranquilizers

When using this product:

Marked drowsiness may occur

Avoid alcoholic beverages

Alcohol, sedatives, and tranquilizers may increase drowsiness

Be careful when driving a motor vehicle or operating machinery

Excitability may occur, especially in children

If pregnant or breast-feeding,ask a health professional before use

Directions

Take every 4 to 6 hours, or as directed by a doctor. Do not take more than 6 times in 24 hours

Adults and children 12 years of age and older: 1 to 2 caplets

Children 6 to 12 years:1 caplet

Children under 6:do not use

Inactive Ingredients

croscarmellose sodium, D C Red 27 aluminum lake, hypromellose, lactose, magnesium stearate, microcystalline cellulose, polyethylene glycol, silicon dioxide, titanium dioxide